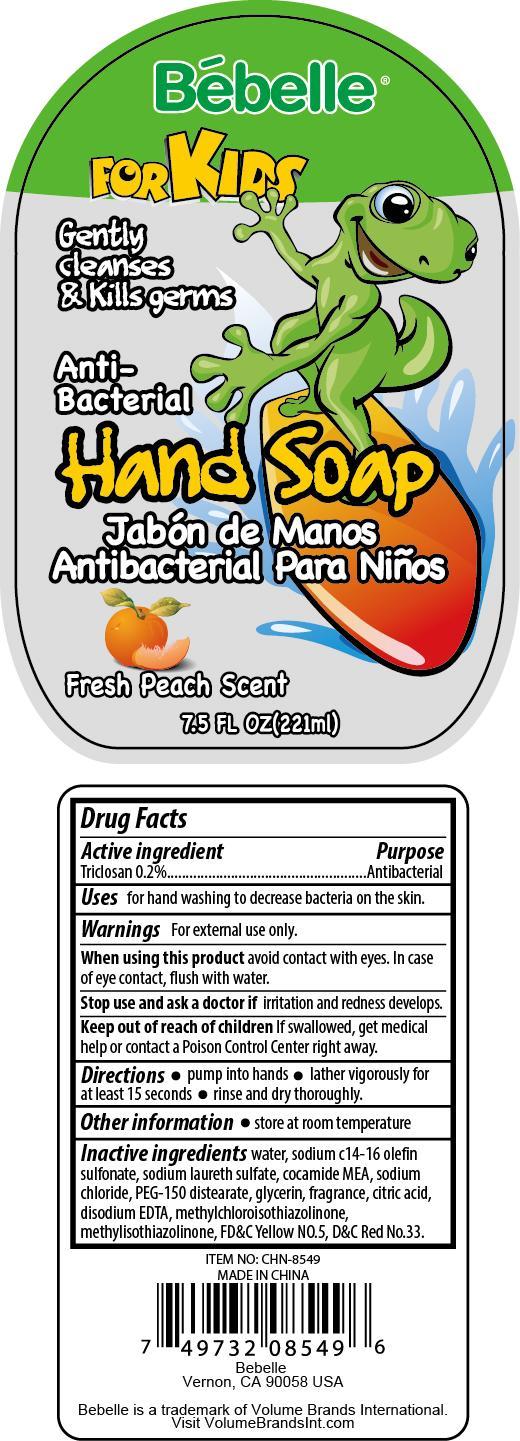 DRUG LABEL: Hand Cleanse
NDC: 58503-086 | Form: SOAP
Manufacturer: China Ningbo Shangge Cosmetic Technology Corp.
Category: otc | Type: HUMAN OTC DRUG LABEL
Date: 20150710

ACTIVE INGREDIENTS: TRICLOSAN 0.2 g/100 g
INACTIVE INGREDIENTS: WATER; SODIUM C14-16 OLEFIN SULFONATE; SODIUM LAURETH SULFATE; COCO MONOETHANOLAMIDE; SODIUM CHLORIDE; PEG-150 DISTEARATE; GLYCERIN; CITRIC ACID MONOHYDRATE; EDETATE DISODIUM; METHYLCHLOROISOTHIAZOLINONE; METHYLISOTHIAZOLINONE; FD&C YELLOW NO. 5; D&C RED NO. 33

Active Ingredient Purpose

Triclosan 0.2% ................. Antibacterial

PURPOSE

Uses For handwashing to decrease bacteria on the skin.

Keep out of reach of children. If swallowed, get medical help or contact a Poison Control Center right away.

INDICATIONS AND USAGE

Bebelle For Kids

Gently cleanses & kills germs

Anti-Bacterial Hand Soap

Jabon de Manos Antibacterial para Ninos

Fresh Peach Scent

Directions

- Pump into hands
- Lather vigorously for at least 15 seconds
- rinse and dry thoroughly

Warnings

For external use only

When using this product, avoid contact with eyes. In case of eye contact, flush with water.

Stop use and ask a dctor if irritation and redness develops.

Inactive Ingredients

water, sodium c14-16 olefin sulfonate, sodium laureth sulfate, cocamide MEA, sodium chloride, PEG-150 distearate, glycerin, fragrance, citric acid, disodium EDTA, methylchloroisothiazolinone, methylisothiazolinone, FD&C yellow no.5, D&C red no.33